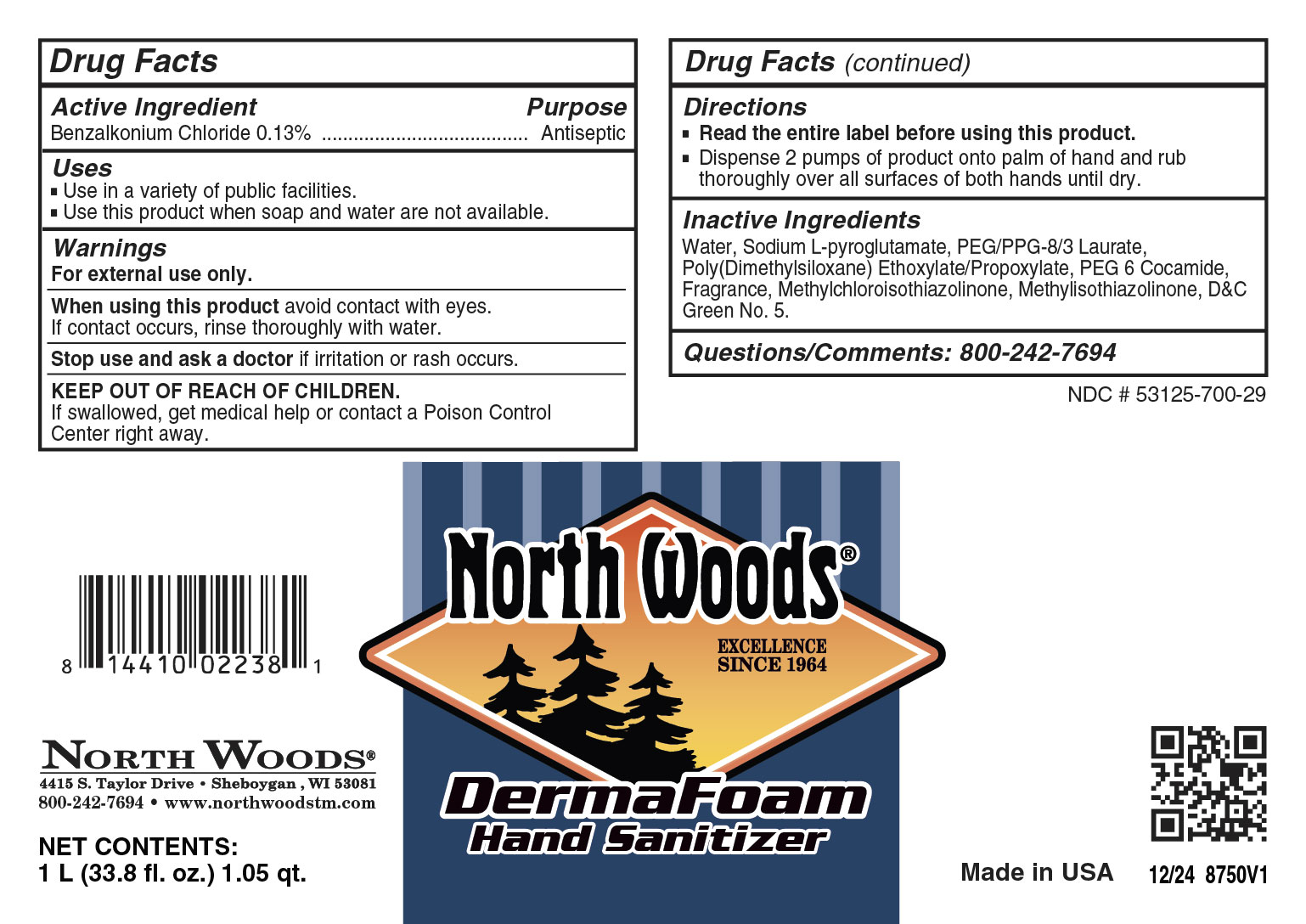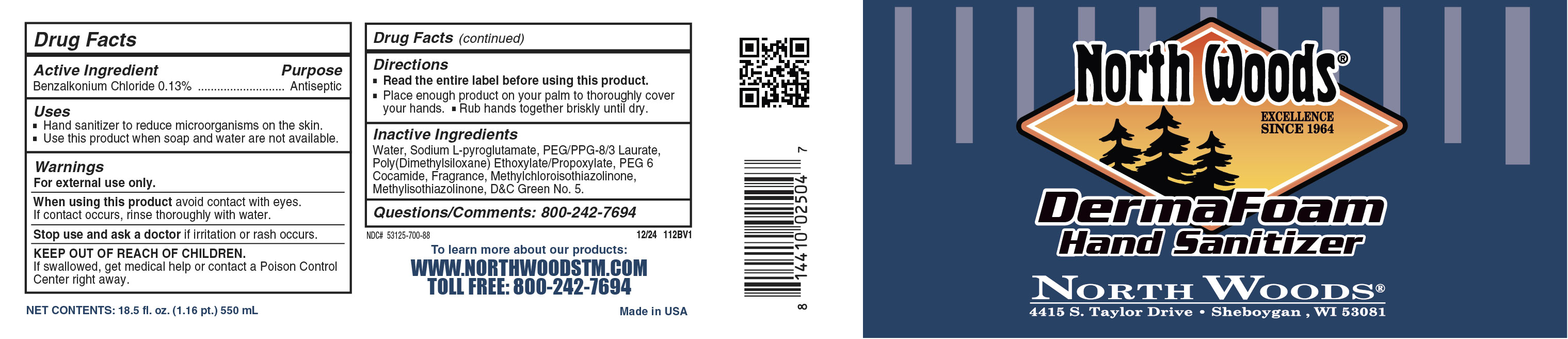 DRUG LABEL: North Woods Derma Foam Hand Sanitizer
NDC: 53125-700 | Form: SOAP
Manufacturer: Superior Chemical Corporation
Category: otc | Type: HUMAN OTC DRUG LABEL
Date: 20251006

ACTIVE INGREDIENTS: BENZALKONIUM CHLORIDE 1.3 mg/1 mL
INACTIVE INGREDIENTS: PEG-9 POLYDIMETHYLSILOXYETHYL DIMETHICONE; DIOXANE; METHYLCHLOROISOTHIAZOLINONE; CYCLOMETHICONE 4; HEXYL SALICYLATE; ALCOHOL; ISOPROPYL ALCOHOL; ACETALDEHYDE; LIME OIL; LEMON OIL; MAGNESIUM NITRATE; HEXAMETHYLINDANOPYRAN; MYRCENE; DIHYDROMYRCENOL; METHYL DIHYDROJASMONATE (SYNTHETIC); LINALOOL, (+/-)-; BUTYLPHENYL METHYLPROPIONAL; WATER; GERANIOL; SODIUM PIDOLATE; GRAPEFRUIT OIL; ORANGE OIL; PEG/PPG-15/15 ALLYL ETHER ACETATE; PEG-6 COCAMIDE; N-ALKYL DIMETHYL BENZYL AMMONIUM CHLORIDE (C12-C18); METHYLISOTHIAZOLINONE; .BETA.-CITRONELLOL, (+/-)-; D&C GREEN NO. 5; SODIUM PCA

North Woods Derma Foam Hand Sanitizer

Active Ingredient

Benzalkonium Chloride 0.13%

Uses

- Use in a variety of public facilities.
- Use this product when soap and water are not available.

Warnings

- For external use only.
- Avoid contact with eyes.
- Children under the age of 6 should be supervised by an adult when using this product.
- Discontinue use is irritation or redness develops.
- If irritation persists for more than 72 hours, consult a physician.
- KEEP OUT OF REACH OF CHILDREN.

Directions

- Read the entire label before using this product.
- Dispense product onto dry hands. Rub hands together until hands are dry.
- Use as needed between hand washes to reduce bacteria on the skin.

Inactive Ingredients

Deionized Water, Sodium PCA, PEG/PPG-8/3 Laurate, Dimethicone, DMDM Hydantoin, PEG-3 Cocamide, Fragrance, Iodoproynyl Btylcarbamate, D&C Green #5.

Questions or Comments? Phone: (800) 777-9343

MDS information:(800) 891-4965

Purpose

Antiseptic

KEEP OUT OF REACH OF CHILDREN